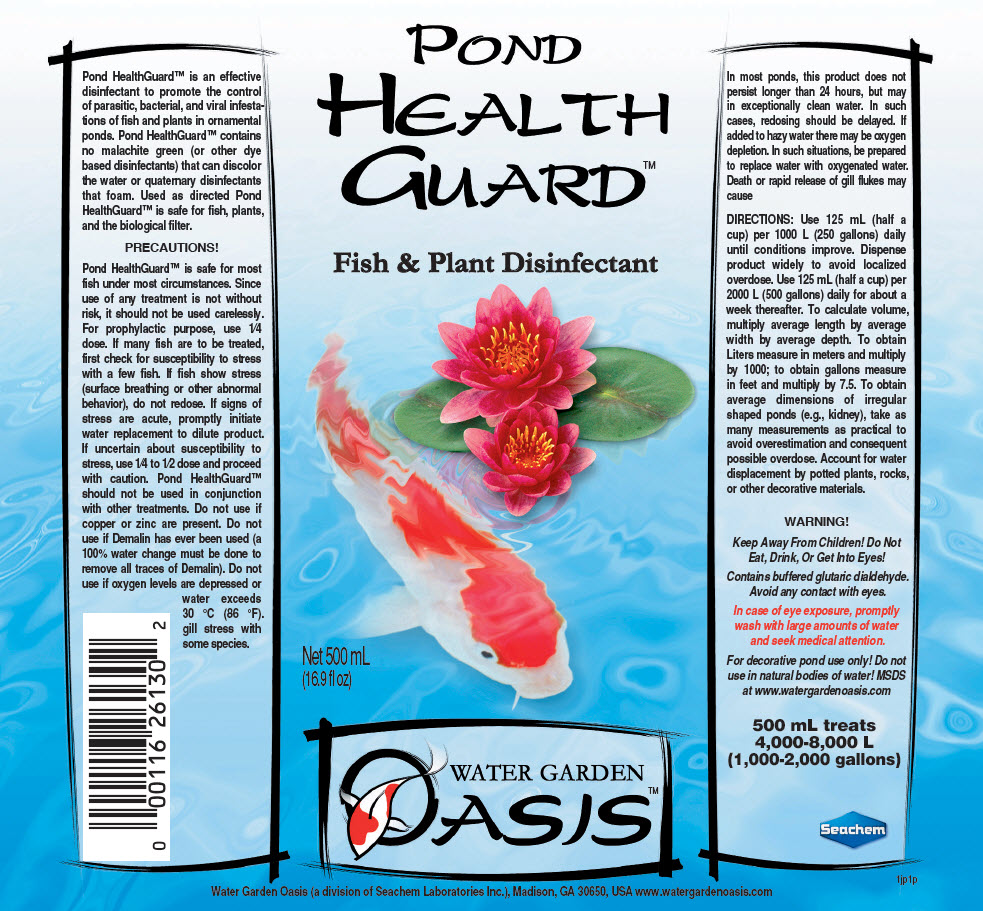 DRUG LABEL: Pond Health Guard
NDC: 55999-136 | Form: LIQUID
Manufacturer: Seachem Laboratories Inc.
Category: animal | Type: OTC ANIMAL DRUG LABEL
Date: 20190821

ACTIVE INGREDIENTS: GLUTARAL 25 mg/1 mL

Pond Health Guard™

INDICATIONS AND USAGE

Pond HealthGuard™ is an effective disinfectant to promote the control of parasitic, bacterial, and viral infestations of fish and plants in ornamental ponds. Pond HealthGuard™ contains no malachite green (or other dye based disinfectants) that can discolor the water or quaternary disinfectants that foam. Used as directed Pond HealthGuard™ is safe for fish, plants, and the biological filter.

PRECAUTIONS!

Pond HealthGuard™ is safe for most fish under most circumstances. Since use of any treatment is not without risk, it should not be used carelessly. For prophylactic purpose, use 1⁄4 dose. If many fish are to be treated, first check for susceptibility to stress with a few fish. If fish show stress (surface breathing or other abnormal behavior), do not redose. If signs of stress are acute, promptly initiate water replacement to dilute product. If uncertain about susceptibility to stress, use 1⁄4 to 1⁄2 dose and proceed with caution. Pond HealthGuard™ should not be used in conjunction with other treatments. Do not use if copper or zinc are present. Do not use if Demalin has ever been used (a 100% water change must be done to remove all traces of Demalin). Do not use if oxygen levels are depressed or water exceeds 30 °C (86 °F). gill stress with some species.

In most ponds, this product does not persist longer than 24 hours, but may in exceptionally clean water. In such cases, redosing should be delayed. If added to hazy water there may be oxygen depletion. In such situations, be prepared to replace water with oxygenated water. Death or rapid release of gill flukes may cause

DOSAGE AND ADMINISTRATION

DIRECTIONS: Use 125 mL (half a cup) per 1000 L (250 gallons) daily until conditions improve. Dispense product widely to avoid localized overdose. Use 125 mL (half a cup) per 2000 L (500 gallons) daily for about a week thereafter. To calculate volume, multiply average length by average width by average depth. To obtain Liters measure in meters and multiply by 1000; to obtain gallons measure in feet and multiply by 7.5. To obtain average dimensions of irregular shaped ponds (e.g., kidney), take as many measurements as practical to avoid overestimation and consequent possible overdose. Account for water displacement by potted plants, rocks, or other decorative materials.

WARNING!

Keep Away From Children! Do Not Eat, Drink, Or Get Into Eyes!

Contains buffered glutaric dialdehyde. Avoid any contact with eyes.

In case of eye exposure, promptly wash with large amounts of water and seek medical attention.

For decorative pond use only! Do not use in natural bodies of water! MSDS at www.watergardenoasis.com

500 mL treats
4,000-8,000 L
(1,000-2,000 gallons)

Seachem

1jp1p

PRINCIPAL DISPLAY PANEL - 500 mL Bottle Label

POND
HEALTH
GUARD™

Fish & Plant Disinfectant

Net 500 mL
(16.9 fl oz)

WATER GARDEN
OASIS™

Water Garden Oasis (a division of Seachem Laboratories Inc.), Madison, GA 30650, USA www.watergardenoasis.com